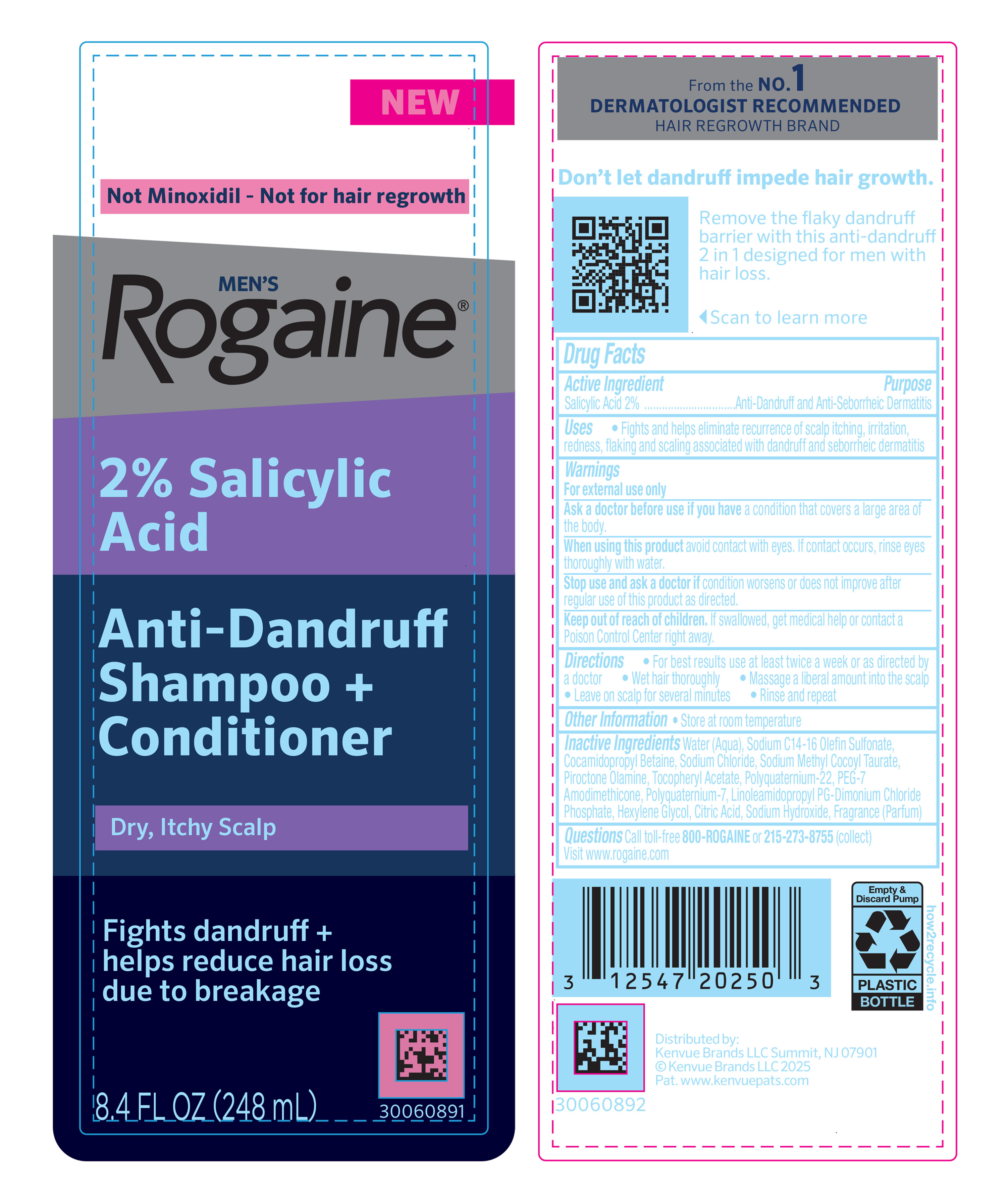 DRUG LABEL: Mens Rogaine 2% Salicylic Acid Anti-Dandruff Plus Conditioner
NDC: 69968-0954 | Form: SHAMPOO
Manufacturer: Kenvue Brands LLC
Category: otc | Type: HUMAN OTC DRUG LABEL
Date: 20260102

ACTIVE INGREDIENTS: SALICYLIC ACID 20 mg/1 mL
INACTIVE INGREDIENTS: SODIUM HYDROXIDE; HEXYLENE GLYCOL; POLYQUATERNIUM-7; LINOLEAMIDOPROPYL PG-DIMONIUM CHLORIDE PHOSPHATE; SODIUM CHLORIDE; ALPHA-TOCOPHEROL ACETATE; SODIUM METHYL COCOYL TAURATE; CITRIC ACID; WATER; SODIUM C14-16 OLEFIN SULFONATE; COCAMIDOPROPYL BETAINE; PIROCTONE OLAMINE

Men’s Rogaine 2% Salicylic Acid Anti-Dandruff Shampoo Plus Conditioner

Drug Facts

Active ingredient

Salicylic Acid 2%

Purpose

Anti-Dandruff and Anti-Seborrheic Dermatitis

Uses

▪ Fights and helps eliminate recurrence of scalp itching, irritation, redness, flaking and scaling associated with dandruff and seborrheic dermatitis.

Warnings

For external use only.

Ask a doctor before use if you have a condition that covers a large area of the body.

When using this product avoid contact with eyes. If contact occurs, rinse eyes thoroughly with water.

Stop use and ask a doctor if condition worsens or does not improve after regular use of this product as directed.

Keep out of reach of children. If swallowed, get medical help or contact a Poison Control Center right away.

Directions

▪ For best results use at least twice a week or as directed by a doctor

▪ Wet hair thoroughly

▪ Massage a liberal amount into the scalp

▪ Leave on scalp for several minutes

▪ Rinse and repeat

Other information

▪ Store at room temperature.

Inactive ingredients

Water (Aqua), Sodium C14-16 Olefin Sulfonate, Cocamidopropyl Betaine, Sodium Chloride, Sodium Methyl Cocoyl Taurate, Piroctone Olamine, Tocopheryl Acetate, Polyquaternium-22, PEG-7 Amodimethicone, Polyquaternium-7, Linoleamidopropyl PG-Dimonium Chloride Phosphate, Hexylene Glycol, Citric Acid, Sodium Hydroxide, Fragrance (Parfum)

Questions

Call toll-free 800-ROGAINE or 215-273-8755 (collect)

Visit www.rogaine.com

Distributed by:

Kenvue Brands LLC,
Summit, NJ 07901

PRINCIPAL DISPLAY PANEL - 248 mL Bottle Pump

NEW

Not Minoxidil – Not for hair regrowth

MEN’S

Rogaine®

2% Salicylic

Acid

Anti-Dandruff

Shampoo +

Conditioner

Dry, Itchy Scalp

Fights dandruff +

helps reduce hair loss

due to breakage

8.4 FL OZ (248 mL)